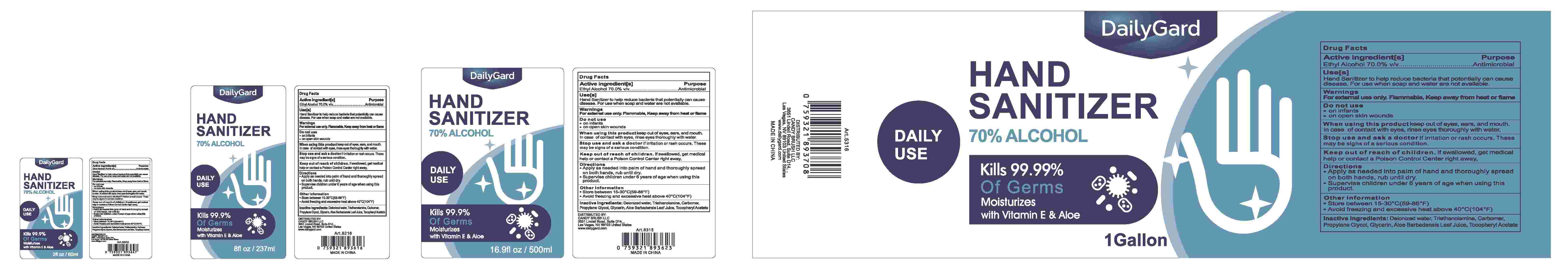 DRUG LABEL: Hand Sanitizer
NDC: 58503-803 | Form: GEL
Manufacturer: China Ningbo Shangge Cosmetic Technology Corp.
Category: otc | Type: HUMAN OTC DRUG LABEL
Date: 20200610

ACTIVE INGREDIENTS: ALCOHOL 75 mL/100 mL
INACTIVE INGREDIENTS: ALOE VERA LEAF; GLYCERIN; CARBOMER HOMOPOLYMER, UNSPECIFIED TYPE; WATER; .ALPHA.-TOCOPHEROL SUCCINATE, D-; TROLAMINE; PROPYLENE GLYCOL

Hand Sanitizer

Active Ingredient(s)

Ethyl Alcohol 70.0%V/v

Purpose

Antimicrobial

Use

Hand Sanitizer to help reduce bacteria that potentially can cause disease. For use when soap and water are not avaliable.

Warnings

For external use only
Flammable, keep away from heat and flame.

Do not use

● on infants
● on open skin wounds

WHEN USING

/

Stop use, and ask a doctor if irritation and redness develop and persistfor more than 72 hours.

Keep out of reach of children. If swallowed. get medical help or contact a Poison Control Center right away.

Directions

● Apply as needed into palm of hand and thoroughly spread on both hands, rub until dry.
● Supervise children under 6 years of age when using this product.

Other information

● Store between15-30°c(59-86°F)
● Avoid freezing and excessive heat above40°c(104°F)

Inactive ingredients

Deionized water, Triethanolamine, Carbomer,Propylene Glycol, Glycerin, Aloe Barbadensis Leaf Juice, Tocophe Acetate